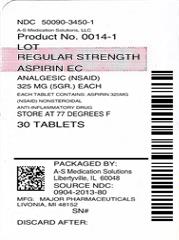 DRUG LABEL: Regular Strength Aspirin EC
NDC: 50090-3450 | Form: TABLET, DELAYED RELEASE
Manufacturer: A-S Medication Solutions
Category: otc | Type: HUMAN OTC DRUG LABEL
Date: 20200118

ACTIVE INGREDIENTS: ASPIRIN 325 mg/1 1
INACTIVE INGREDIENTS: STARCH, CORN; CROSCARMELLOSE SODIUM; D&C YELLOW NO. 10; FD&C YELLOW NO. 6; HYPROMELLOSE 2910 (6 MPA.S); HYPROMELLOSE 2910 (15 MPA.S); METHACRYLIC ACID - ETHYL ACRYLATE COPOLYMER (1:1) TYPE A; MICROCRYSTALLINE CELLULOSE; MINERAL OIL; POLYSORBATE 80; SILICON DIOXIDE; DIMETHICONE; SODIUM HYDROXIDE; SODIUM LAURYL SULFATE; TALC; TITANIUM DIOXIDE; TRIETHYL CITRATE

Drug Facts

Active ingredient

- Active ingredient (in each tablet) Purpose
Aspirin 325 mg (NSAID*).............................Pain reliever
*nonsteroidal anti-inflammatory drug

Purpose

  Pain reliever

Uses

  - for the temporary relief of minor aches and pains due to
    - headache
    - colds
    - muscle pain
    - menstrual pain
    - toothache
    - minor pain of arthritis
  - or as directed by your doctor

Warnings

  Reye's syndrome: Children and teenagers who have or are recovering from chicken pox or flu-like symptoms should not use this product. When using this product, if changes in behavior with nausea or vomiting occur, consult a doctor because these symptoms could be an early sign of Reye's syndrome, a rare but serious illness.
  Allergy alert: Aspirin may cause a severe allergic reaction, which may include:
  - hives
  - facial swelling
  - shock
  - asthma (wheezing)
Stomach bleeding warning: This product contains an NSAID, which may cause severe stomach bleeding. The chance is higher if you:
  1. are age 60 or older
  2. have had stomach ulcers or bleeding problems
  3. take a blood thinning (anticoagulant) or steroid drug
  4. take other drugs containing prescription or nonprescription NSAIDs (aspirin, ibuprofen, naproxen, or others)
  5. have 3 or more alcoholic drinks every day while using this product
  6. take more or for a longer time than directed

Do Not Use

  - if you are allergic to aspirin or any other pain reliever/fever reducer

Ask Doctor

- Ask a doctor before use if
  - stomach bleeding warning applies to you
  - you have a history of stomach problems, such as heartburn
  - you have high blood pressure, heart disease, liver cirrhosis, or kidney disease
  - you are taking a diuretic
  - you have asthma
  - you have not been drinking fluids

Ask Doctor/Pharmacist

- Ask a doctor or pharmacist before use if you are
  - taking a prescription drug for diabetes, gout, or arthritis
  - taking any other drugs
  - under a doctor's care for any serious condition

Stop Use

- Stop use and ask a doctor if
  - you experience any of the following signs of stomach bleeding:
    - feel faint
    - have bloody or black stools
    - vomit blood
    - have stomach pain that does not get better
  - pain gets worse or lasts more than 10 days
  - fever gets worse or lasts more than 3 days
  - redness or swelling is present in the painful area
  - any new symptoms appear
  - ringing in the ears or a loss of hearing occurs

Pregnancy or Breast Feeding

If pregnant or breast-feeding, ask a health professional before use. It is especially important not to use aspirin during the last 3 months of pregnancy unless definitely directed to do so by a doctor because it may cause problems in the unborn child or complications during delivery.

Directions

  - drink a full glass of water with each dose
  - adults and children 12 years and over: take 1 to 2 tablets every 4 hours while symptoms last. Do not take more than 12 tablets in 24 hours unless directed by a doctor
  - children under 12 years: consult a doctor

Keep out of reach of children. In case of overdose, get medical help or contact a Poison Control Center right away (1-800-222-1222).

Storage and Handling

- Other information
  - store at 25°C (77°F) excursions permitted between 15°-30°C (59°-86°F)
  - use by expiration date on package

Inactive Ingredients

Inactive ingredients corn starch, croscarmellose sodium, D-C yellow #10 aluminum lake, FD-C yellow #6 aluminum lake, hypromellose, methacrylic acid copolymer, microcrystalline cellulose, mineral oil, polysorbate 80, simethicone, sodium hydroxide, sodium lauryl sulfate, talc, titanium dioxide, triethyl citrate

Questions

Questions? To Report Adverse Drug Event Call: (800) 616-2471

HOW SUPPLIED

Product: 50090-3450

NDC: 50090-3450-1 30 TABLET, DELAYED RELEASE in a BOTTLE